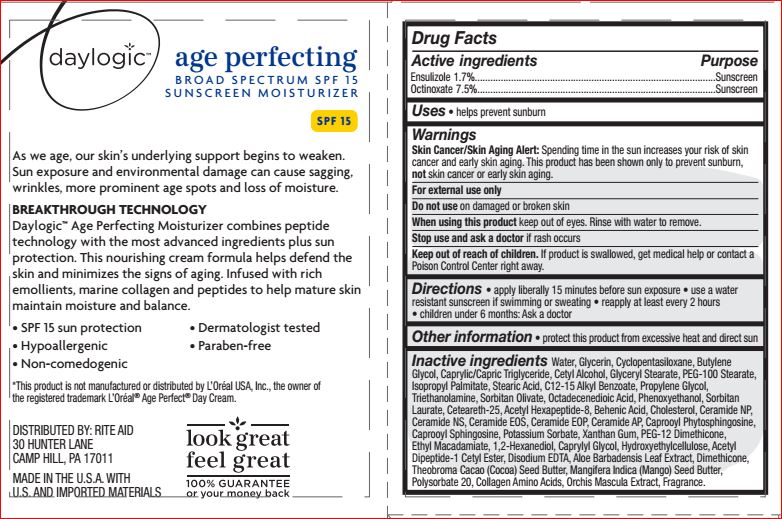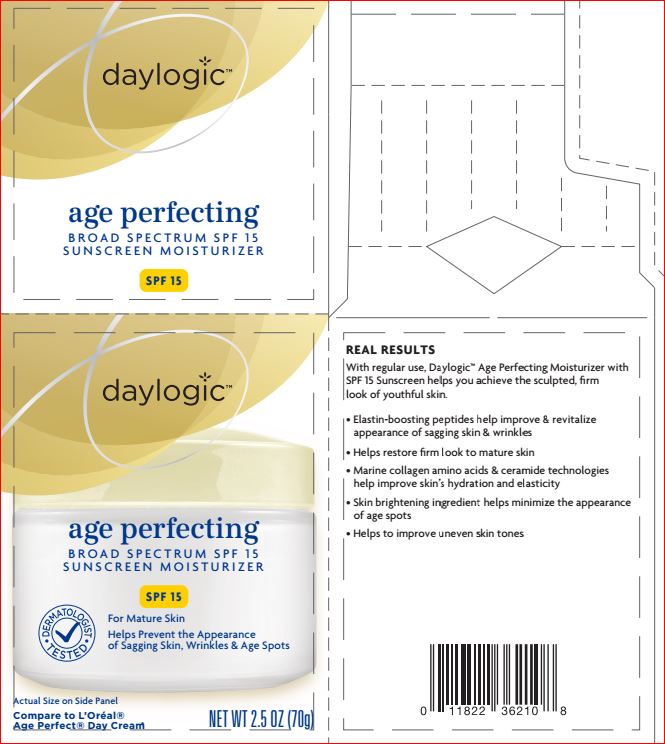 DRUG LABEL: Age Perfecting SPF 15 Sunscreen

NDC: 11822-2222 | Form: CREAM
Manufacturer: Rite Aid
Category: otc | Type: HUMAN OTC DRUG LABEL
Date: 20180102

ACTIVE INGREDIENTS: ENSULIZOLE 1.7 g/100 g; OCTINOXATE 7.5 g/100 g
INACTIVE INGREDIENTS: WATER; GLYCERIN; CYCLOMETHICONE 5; BUTYLENE GLYCOL; MEDIUM-CHAIN TRIGLYCERIDES; CETYL ALCOHOL; GLYCERYL MONOSTEARATE; PEG-100 STEARATE; ISOPROPYL PALMITATE; STEARIC ACID; ALKYL (C12-15) BENZOATE; PROPYLENE GLYCOL; TROLAMINE; SORBITAN OLIVATE; OCTADECENEDIOIC ACID; PHENOXYETHANOL; SORBITAN MONOLAURATE; CETEARETH-25; ACETYL HEXAPEPTIDE-8; BEHENIC ACID; CHOLESTEROL; CERAMIDE NP; CERAMIDE NG; CERAMIDE EOS; CERAMIDE 1; CERAMIDE AP; POTASSIUM SORBATE; XANTHAN GUM; PEG-12 DIMETHICONE; ETHYL MACADAMIATE; 1,2-HEXANEDIOL; CAPRYLYL GLYCOL; ACETYL TYROSYLARGININE CETYL ESTER

Drug Facts

Active ingredients Purpose

Ensulizole - 1.70% Sunscreen
Octinoxate - 7.50% Sunscreen

INDICATIONS AND USAGE

- helps prevent sunburn
- if used as directed with other sun protection messures (see Directions) decreases the risk of skin cancer and early skin aging caused by sun.

Warnings

For external use only
Do not use on damaged or broken skin
When using this product keep out of eyes. Rinse with water to remove.
Stop use and ask a doctor if rash occurs
Keep out of reach of children. If product is swallowed, get medical help or contact a Poison Control Center right away.

Directions

apply liberally 15 minutes before sun exposure
• reapply: • after 80 minutes of swimming or sweating
• immediately after towel drying • at least every 2 hours
• Sun Protection Measures. Spending time in the sun
increases your risk of skin cancer and early skin aging.
To decrease this risk, regularly use a sunscreen with a
broad spectrum SPF of 15 or higher and other sun
protection measures including:
• limit time in the sun, especially from 10 a.m. – 2 p.m.
• wear long-sleeve shirts, pants, hats, and sunglasses
• children under 6 months: Ask a doctor

Inactive ingredients

Water
Glycerin
Cyclopentasiloxane
Butylene Glycol
Caprylic/Capric Triglyceride
Cetyl Alcohol
Glyceryl Stearate
PEG-100 Stearate
Isopropyl Palmitate
Stearic Acid
C12-15 Alkyl Benzoate
Propylene Glycol
Triethanolamine
Sorbitan Olivate
Octadecenedioic Acid
Phenoxyethanol
Sorbitan Laurate
Ceteareth-25
Acetyl Hexapeptide-8
Behenic Acid
Cholesterol
Ceramide NP
Ceramide NS
Ceramide EOS
Ceramide EOP
Ceramide AP
Caprooyl Phytosphingosine
Caprooyl Sphingosine
Potassium Sorbate
Xanthan Gum
PEG-12 Dimethicone
Ethyl Macadamiate
1,2-Hexanediol
Caprylyl Glycol
Hydroxyethylcellulose
Acetyl Dipeptide-1 Cetyl Ester